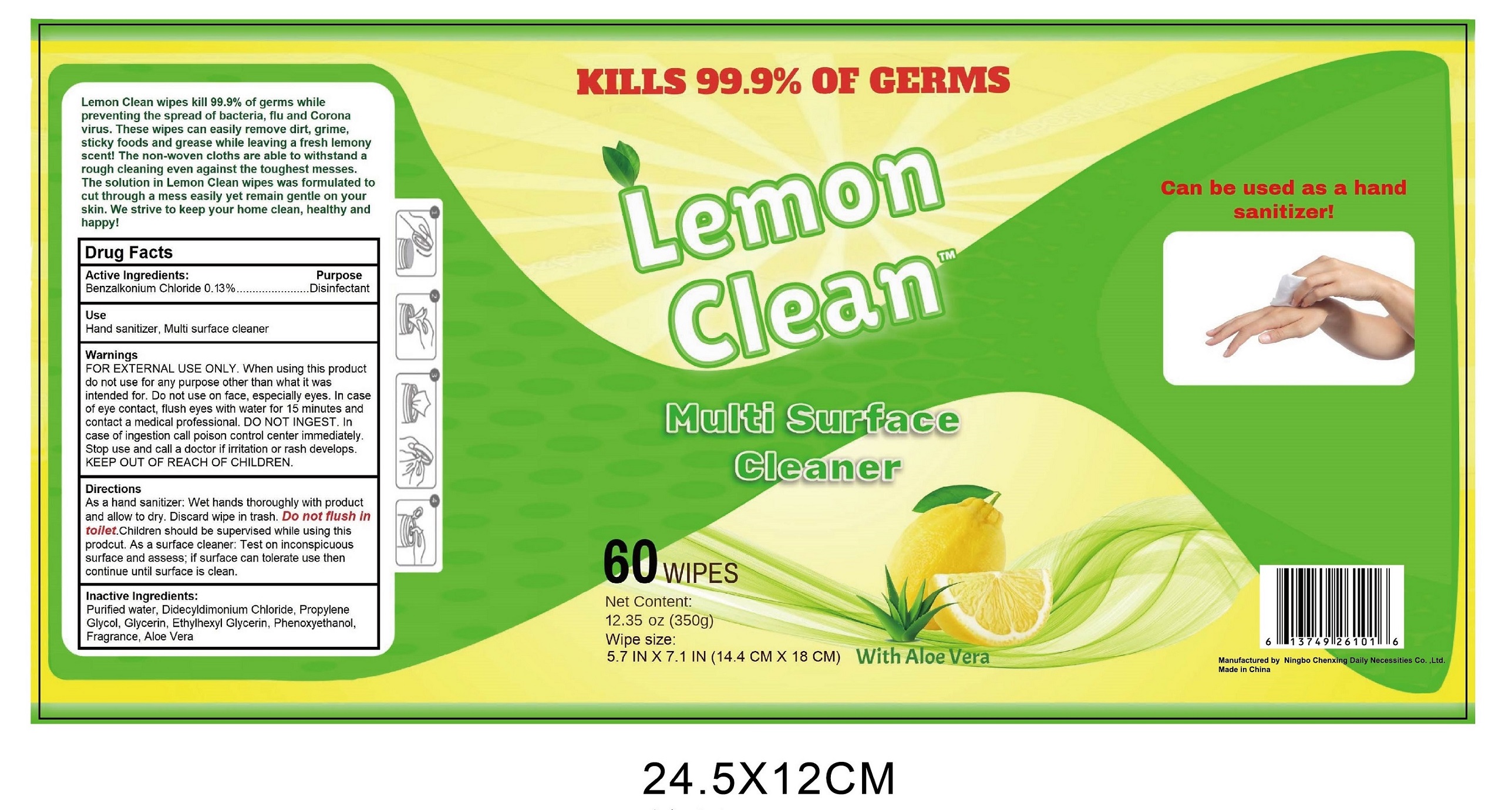 DRUG LABEL: Lemon clean
NDC: 75662-060 | Form: CLOTH
Manufacturer: Ningbo Chenxing Daily Necessities Co., Ltd.
Category: otc | Type: HUMAN OTC DRUG LABEL
Date: 20201214

ACTIVE INGREDIENTS: BENZALKONIUM CHLORIDE 0.13 g/100 g
INACTIVE INGREDIENTS: LEMON; ETHYLHEXYLGLYCERIN; ALOE; DIDECYLDIMONIUM CHLORIDE; WATER; PROPYLENE GLYCOL; GLYCERIN; PHENOXYETHANOL

75662-060 Lemon clean Wet Wipes Ningbo Chenxing Daily Necessities Co., Ltd.

Active Ingredient(s)

Benzalkonium Chloride 0.13%. Purpose: Disinfectant

Purpose

Disinfectant, Wet Wipes

Use

Hand sanitizer, Multi surface cleaner.

Warnings

FOR EXTERNAL USE ONLY.

When using this product do not use for any purpose other than what is was intended for.

Do not use on face, especially eyes.

In case of eye contact, flush eyes with water for 15 minutes and contact a medical professional.

DO NOT INGEST.

In case of ingestion call poison control center immediately.

Stop use and call a docotor if irritation or rash develops.

KEEP OUT OF REACH OF CHILDREN.

Do not use on face, especially eyes.

In case of eye contact, flush eyes with water for 15 minutes and contact a medical professional.

DO NOT INGEST.

In case of ingestion call poison control center immediately.

When using this product do not use for any purpose other than what is was intended for.

STOP USE

In case of ingestion call poison control center immediately.

Stop use and call a docotor if irritation or rash develops.

KEEP OUT OF REACH OF CHILDREN.

Keep out of reach of children. If swallowed, get medical help or contact a Poison Control Center right away.

Directions

As a hand sanitizer. Wet hands thoroughly with product and allow to dry. Discard wipe in trash.

Do not flush in toilet. Children should be supervised while using this product.

As a surface cleaner: Test on inconspicuous surface and assess; If surface can tolerate use then continue until surface is clean.

Other information

Keep containers tightly closed in a dry, cool and well-ventilated place.

Recommended storage temperature: 0℃ to 40℃.

Inactive ingredients

Purkfied water, Didecyldimonium Chloride, Propylene Glycol, Glycerin, Ethylhexyl Glycerin, Phenoxyethanol, Fragrance, Aloe Vera